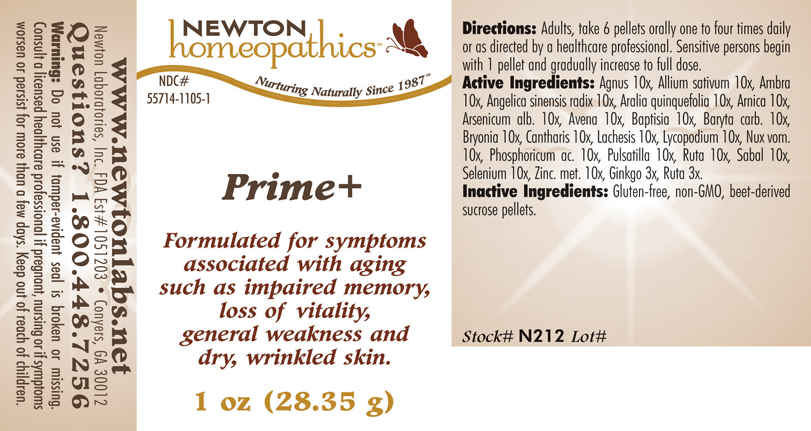 DRUG LABEL: Prime Plus 
NDC: 55714-1105 | Form: PELLET
Manufacturer: Newton Laboratories, Inc.
Category: homeopathic | Type: HUMAN OTC DRUG LABEL
Date: 20110301

ACTIVE INGREDIENTS: Chaste Tree 10 [hp_X]/1 g; Garlic 10 [hp_X]/1 g; Ambergris 10 [hp_X]/1 g; Angelica Sinensis Root 10 [hp_X]/1 g; American Ginseng 10 [hp_X]/1 g; Arnica Montana 10 [hp_X]/1 g; Arsenic Trioxide 10 [hp_X]/1 g; Avena Sativa Flowering Top 10 [hp_X]/1 g; Baptisia Tinctoria Root 10 [hp_X]/1 g; Barium Carbonate 10 [hp_X]/1 g; Bryonia Alba Root 10 [hp_X]/1 g; Lytta Vesicatoria 10 [hp_X]/1 g; Lachesis Muta Venom 10 [hp_X]/1 g; Lycopodium Clavatum Spore 10 [hp_X]/1 g; Strychnos Nux-vomica Seed 10 [hp_X]/1 g; Phosphoric Acid 10 [hp_X]/1 g; Pulsatilla Vulgaris 10 [hp_X]/1 g; Ruta Graveolens Flowering Top 10 [hp_X]/1 g; Saw Palmetto 10 [hp_X]/1 g; Selenium 10 [hp_X]/1 g; Zinc 10 [hp_X]/1 g; Ginkgo 3 [hp_X]/1 g
INACTIVE INGREDIENTS: Sucrose

Prime +

INDICATIONS AND USAGE SECTION

Prime+ Formulated for symptoms associated with aging such as impaired memory, loss of vitality, general weakness and dry, wrinkled skin.

DOSAGE AND ADMINISTRATION SECTION

Directions: Adults, take 6 pellets orally one to four times daily or as directed by a healthcare professional. Sensitive persons begin with 1 pellet and gradually increase to full dose.

OTC ACTIVE INGREDIENT SECTION

Agnus 10x, Allium sativum 10x, Ambra10x, Angelica sinensis radix 10x, Aralia quinquefolia 10x, Arnica 10x, Arsenicum alb. 10x, Avena 10x, Baptisia 10x, Baryta carb. 10x, Bryonia 10x, Cantharis 10x, Lachesis 10x, Lycopodium 10x, Nux vom.10x, Phosphoricum ac. 10x, Pulsatilla 10x, Ruta 10x, Sabal 10x, Selenium 10x, Zinc. met. 10x, Ginkgo 3x, Ruta 3x.

OTC PURPOSE SECTION

Formulated for symptoms associated with aging such as impaired memory, loss of vitality, general weakness and dry, wrinkled skin.

INACTIVE INGREDIENT SECTION

Inactive Ingredients: Gluten-free, non-GMO, beet-derived sucrose pellets.

QUESTIONS? SECTION

www.newtonlabs.net Newton Laboratories, Inc. FDA Est # 1051203 - Conyers, GA 30012
Questions? 1.800.448.7256

WARNINGS SECTION

Warning: Do not use if tamper - evident seal is broken or missing. Consult a licensed healthcare professional if pregnant, nursing or if symptoms worsen or persist for more than a few days. Keep out of reach of children

OTC - PREGNANCY OR BREAST FEEDING SECTION

Consult a licensed healthcare professional if pregnant, nursing or if symptoms worsen or persist for more than a few days.

OTC - KEEP OUT OF REACH OF CHILDREN SECTION

Keep out of reach of children.